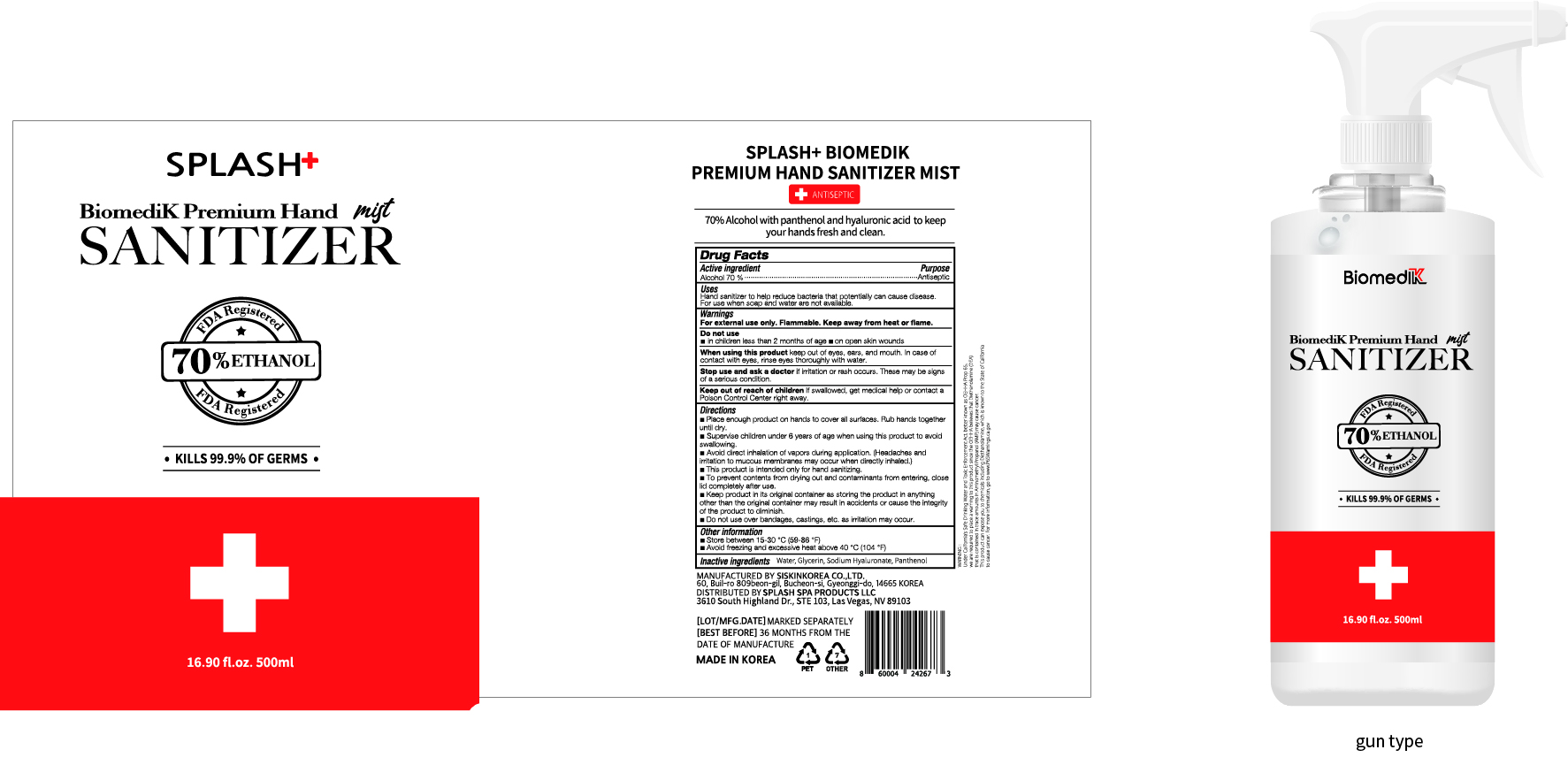 DRUG LABEL: BiomediK Premium Hand Sanitizer mist
NDC: 74514-0502 | Form: SPRAY
Manufacturer: SISKINKOREA CO.,LTD.
Category: otc | Type: HUMAN OTC DRUG LABEL
Date: 20200708

ACTIVE INGREDIENTS: ALCOHOL 350 mL/500 mL
INACTIVE INGREDIENTS: GLYCERIN; PANTHENOL; WATER; HYALURONATE SODIUM

BiomediK Premium Hand Sanitizer mist | Bottle+Gun type Spray | 74514-0502-1